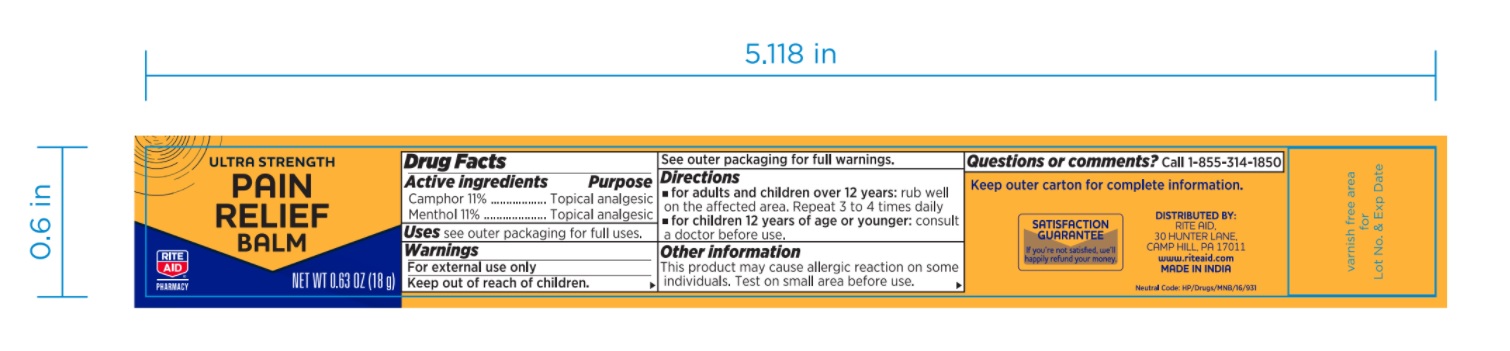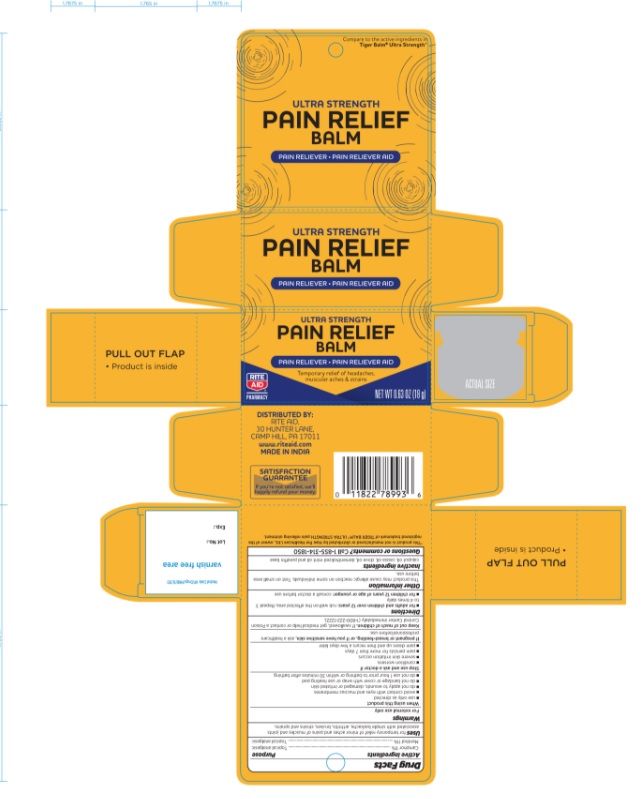 DRUG LABEL: Ultra strength pain relief balm

NDC: 76168-331 | Form: OINTMENT
Manufacturer: Velocity Pharma LLC
Category: otc | Type: HUMAN OTC DRUG LABEL
Date: 20221120

ACTIVE INGREDIENTS: CAMPHOR (SYNTHETIC) 110 mg/1 g; MENTHOL, UNSPECIFIED FORM 110 mg/1 g
INACTIVE INGREDIENTS: CAJUPUT OIL; PADANG CASSIA OIL; CLOVE OIL

Ultra strength pain relief balm

Drug Facts

ACTIVE INGREDIENT

Active Ingredients | Purpose
Camphor 11% | Topical Analgesic
Menthol 11% | Topical Analgesic

Uses

See outer packaging for full uses.

Warnings

For External Use Only

When using this product

- Use only as directed
- Avoid contact with eyes and mucous membranes
- Do not apply to wounds, damaged or irritated skin
- Do not bandage or cover with wrap or use heating pad
- Do not use 1 hour prior to bathing or within 30 minutes after bathing.

Stop use and ask a doctor if

- Condition worsens
- Severe skin irritation occurs
- Pain persists for more than 7 days
- Pain clears up and then recurs a few days later.

PREGNANCY OR BREAST FEEDING

If pregnant or breast-feeding, or if you have sensitive skin, ask a healthcare professional before use.

Keep out of reach of children. If swallowed, get medical help or contact a Poison Control Center immediately.

Directions

- For adults and children over 12, rub well on the affected area. Repeat 3 to 4 times daily
- For children 12 years of age or younger, consult a doctor before use.

Other information

This product may cause allergic reaction on some individuals. Test on small area before use.

Inactive Ingredients

Cajuput Oil, Cassia Oil, Clove Oil, Dementholized Mint Oil and Paraffin base.

Questions

1-855-314-1850